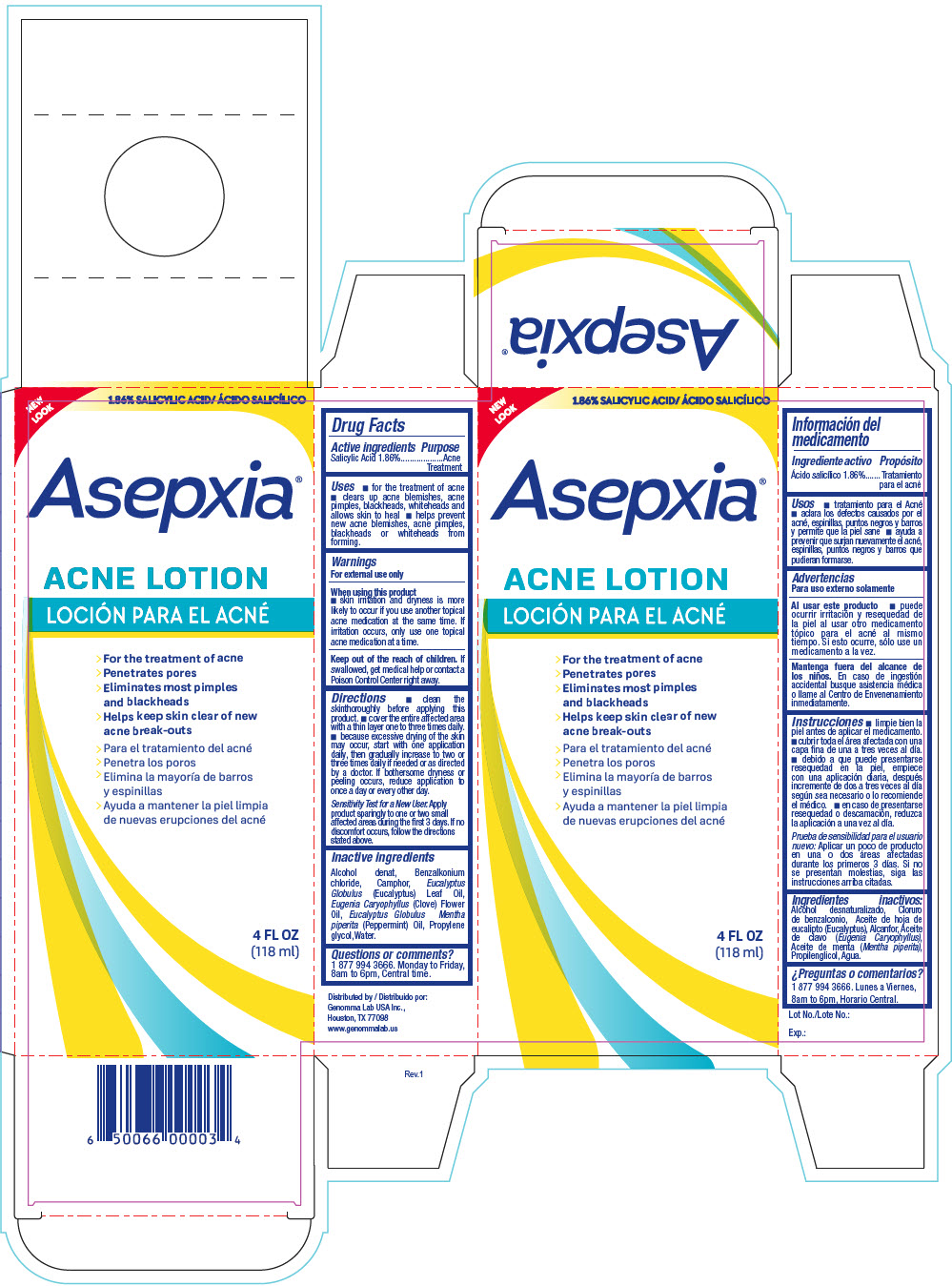 DRUG LABEL: Asepxia Acne
NDC: 50066-063 | Form: LIQUID
Manufacturer: Genomma Lab USA
Category: otc | Type: HUMAN OTC DRUG LABEL
Date: 20241007

ACTIVE INGREDIENTS: SALICYLIC ACID 18.6 mg/1 mL
INACTIVE INGREDIENTS: ALCOHOL; WATER; PROPYLENE GLYCOL; BENZALKONIUM CHLORIDE; CAMPHOR (NATURAL); EUCALYPTUS OIL

Asepxia®Acne Lotion

Drug Facts

Active ingredients

Salicylic Acid 1.86%

Purpose

Acne Treatment

Uses

- for the treatment of acne
- clears up acne blemishes, acne pimples, blackheads, whiteheads and allows skin to heal
- helps prevent new acne blemishes, acne pimples, blackheads or whiteheads from forming.

Warnings

For external use only

When using this product

- skin irritation and dryness is more likely to occur if you use another topical acne medication at the same time. If irritation occurs, only use one topical acne medication at a time.

KEEP OUT OF REACH OF CHILDREN

Keep out of the reach of children.If swallowed, get medical help or contact a Poison Control Center right away.

Directions

- clean the skinthoroughly before applying this product.
- cover the entire affected area with a thin layer one to three times daily.
- because excessive drying of the skin may occur, start with one application daily, then gradually increase to two or three times daily if needed or as directed by a doctor. If bothersome dryness or peeling occurs, reduce application to once a day or every other day.

Sensitivity Test for a New User.Apply product sparingly to one or two small affected areas during the first 3 days. If no discomfort occurs, follow the directions stated above.

Inactive ingredients

Alcohol denat, Benzalkonium chloride, Camphor, Eucalyptus Globulus(Eucalyptus) Leaf Oil, Eugenia Caryophyllus(Clove) Flower Oil, Eucalyptus Globulus Mentha piperita(Peppermint) Oil, Propylene glycol,Water.

Questions or comments?

1 877 994 3666. Monday to Friday, 8am to 6pm, Central time.

Distributed by:
Genomma Lab USA Inc.,
Houston, TX 77098

PRINCIPAL DISPLAY PANEL - 118 ml Bottle Carton

NEW
LOOK

1.86% SALICYLIC ACID

Asepxia®

ACNE LOTION

- For the treatment of acne
- Penetrates pores
- Eliminates most pimples
  and blackheads
- Helps keep skin clear of new
  acne break-outs

4 FL OZ
(118 ml)